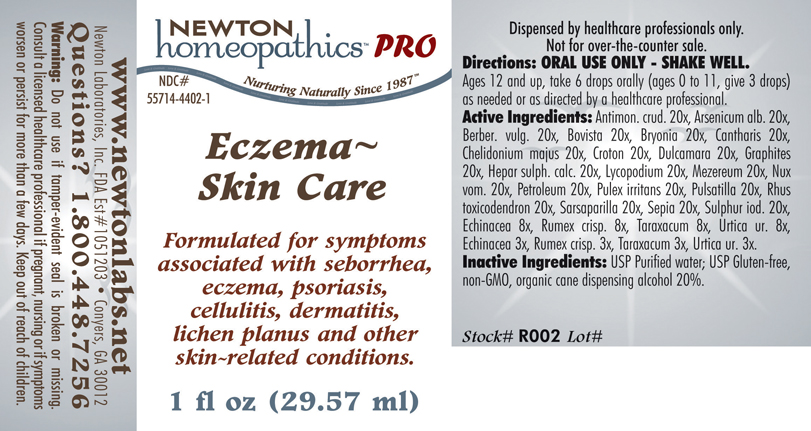 DRUG LABEL: Eczema Skin Care 
NDC: 55714-4402 | Form: LIQUID
Manufacturer: Newton Laboratories, Inc.
Category: homeopathic | Type: HUMAN PRESCRIPTION DRUG LABEL
Date: 20110601

ACTIVE INGREDIENTS: Antimony Trisulfide 20 [hp_X]/1 mL; Arsenic Trioxide 20 [hp_X]/1 mL; Berberis Vulgaris Root Bark 20 [hp_X]/1 mL; Giant Puffball 20 [hp_X]/1 mL; Bryonia Alba Root 20 [hp_X]/1 mL; Lytta Vesicatoria 20 [hp_X]/1 mL; Chelidonium Majus 20 [hp_X]/1 mL; Croton Tiglium Seed 20 [hp_X]/1 mL; Solanum Dulcamara Top 20 [hp_X]/1 mL; Graphite 20 [hp_X]/1 mL; Calcium Sulfide 20 [hp_X]/1 mL; Lycopodium Clavatum Spore 20 [hp_X]/1 mL; Daphne Mezereum Bark 20 [hp_X]/1 mL; Strychnos Nux-vomica Seed 20 [hp_X]/1 mL; Kerosene 20 [hp_X]/1 mL; Pulex Irritans 20 [hp_X]/1 mL; Pulsatilla Vulgaris 20 [hp_X]/1 mL; Toxicodendron Pubescens Leaf 20 [hp_X]/1 mL; Smilax Regelii Root 20 [hp_X]/1 mL; Sepia Officinalis Juice 20 [hp_X]/1 mL; Sulfur Iodide 20 [hp_X]/1 mL; Echinacea Angustifolia 8 [hp_X]/1 mL; Rumex Crispus Root 8 [hp_X]/1 mL; Taraxacum Officinale 8 [hp_X]/1 mL; Urtica Urens 8 [hp_X]/1 mL; Echinacea Angustifolia 3 [hp_X]/1 mL; Rumex Crispus Root 3 [hp_X]/1 mL; Taraxacum Officinale 3 [hp_X]/1 mL; Urtica Urens 3 [hp_X]/1 mL

Eczema Skin Care

PRODUCT NAME & INDICATIONS SECTION

ECZEMA~SKIN CARE Formulated for symptoms associated with seborrhea, eczema, psoriasis, cellulitis, dermatitis, lichen planus and other skin-related conditions.

DIRECTION SECTION

Directions: ORAL USE ONLY - SHAKE WELL. Ages 12 and up, take 6 drops orally (ages 0 to 11, give 3 drops) as needed or as directed by a healthcare professional.

ACTIVE INGREDIENT SECTION

Antimon. crud. 20x, Arsenicum alb. 20x, Berber. vulg. 20x, Bovista 20x, Bryonia 20x, Cantharis 20x, Chelidonium majus 20x, Croton 20x, Dulcamara 20x, Graphites 20x, Hepar sulph. calc. 20x, Lycopodium 20x, Mezereum 20x, Nux vom. 20x, Petroleum 20x, Pulex irritans 20x, Pulsatilla 20x, Rhus toxicodendron 20x, Sarsaparilla 20x, Sepia 20x, Sulphur iod. 20x, Echinacea 8x, Rumex crisp. 8x, Taraxacum 8x, Urtica ur. 8x, Echinacea 3x, Rumex crisp. 3x, Taraxacum 3x, Urtica ur. 3x.

INACTIVE INGREDIENT SECTION

Inactive Ingredients: USP Purified Water; USP Gluten-free, non-GMO, organic cane dispensing alcohol 20%.

QUESTIONS? SECTION

www.newtonlabs.net Newton Laboratories, Inc. FDA Est # 1051203 -Conyers, GA 30012
Questions? 1.800.448.7256

WARNINGS SECTION

Warning: Do not use if tamper- evident seal is broken or missing. Consult a licensed healthcare professional if pregnant, nursing or if symptoms worsen or persist for more than a few days. Keep out of reach of children.

OTC - PREGNANCY OR BREAST FEEDING SECTION

Consult a licensed healthcare professional if pregnant, nursing or if symptoms worsen or persist for more than a few days.

OTC - KEEP OUT OF REACH OF CHILDREN SECTION

Keep out of reach of children.